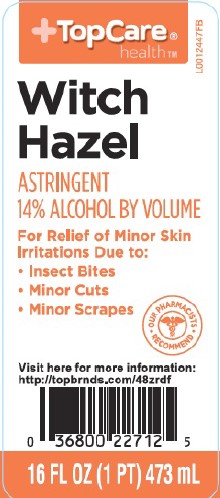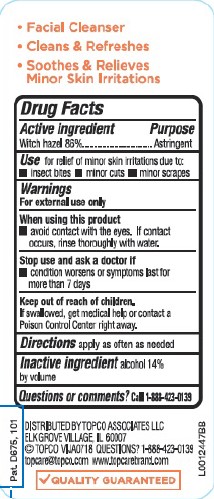 DRUG LABEL: Witch Hazel
NDC: 76162-822 | Form: LIQUID
Manufacturer: Topco Associates LLC
Category: otc | Type: HUMAN OTC DRUG LABEL
Date: 20260213

ACTIVE INGREDIENTS: WITCH HAZEL 860 mg/1 mL
INACTIVE INGREDIENTS: ALCOHOL

Top Care 822.001/822AA
Witch Hazel USP

Claims

- Facial Cleanser
- Cleans & Refreshes
- Soothes & Relieves Minor Skin Irritations

ACTIVE INGREDIENT

Witch hazel 86%

PURPOSE

Astringent

Use

for relief of minor skin irritations due to:
•insect bites • minor cuts •minor scrapes

Warnings

For external use only

When using this product

- avoid contact with the eyes. If contact occurs, rinse thoroughly with water.

Stop use and ask a doctor if

- condition worsens or symptoms persists for more than 7 days

Keep out of reach of children.

If swallowed, get medical help or contact a Poison Control Center right away.

Directions

apply as often as needed

Inactive ingredient

alcohol 14% by volume

Questions or comments?

Call 1-888-423-0139

ADVERSE REACTION

DISTRIBUTED BY TOPCO ASSOCIATES LLC

ELK GROVE VILLAGE, IL 60007

TOPCO VIJA0718 Questions? 1-888-423-0139

topcare @topco.com www.topcarebrand.com

QUALITY GUARANTEED

Pat. D675, 101

principal display panel

TopCare®

health™

Witch

Hazel

Astringent

14% alcohol by volume

For relief of minor skn irritations due to:

- insect bites
- minor cuts
- minor scrapes

OUR PHARMACISTS RECOMMENDED

Visit here for more information:

http://topbrnds.com/48zrdf

16 FL OZ (1PT) 473 mL